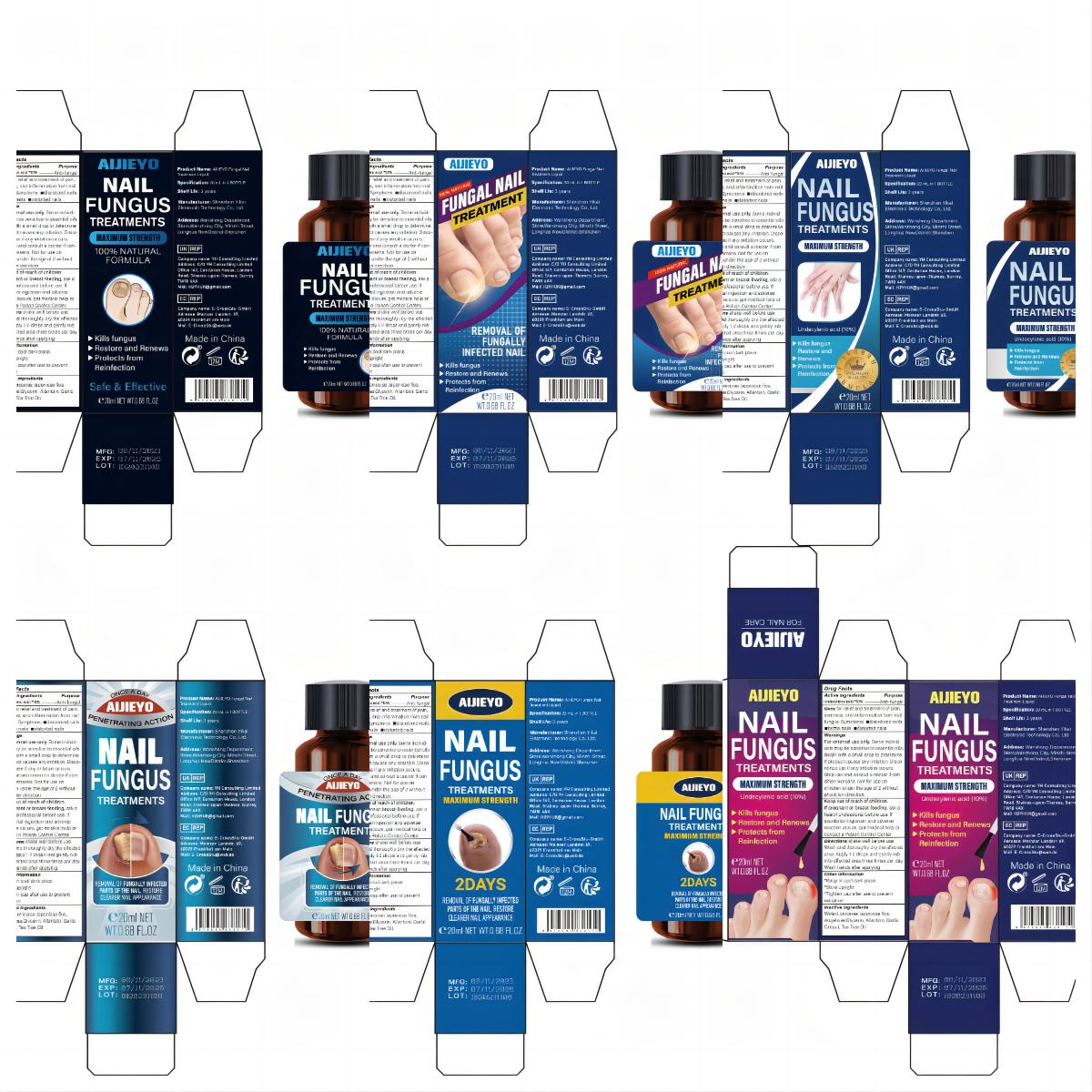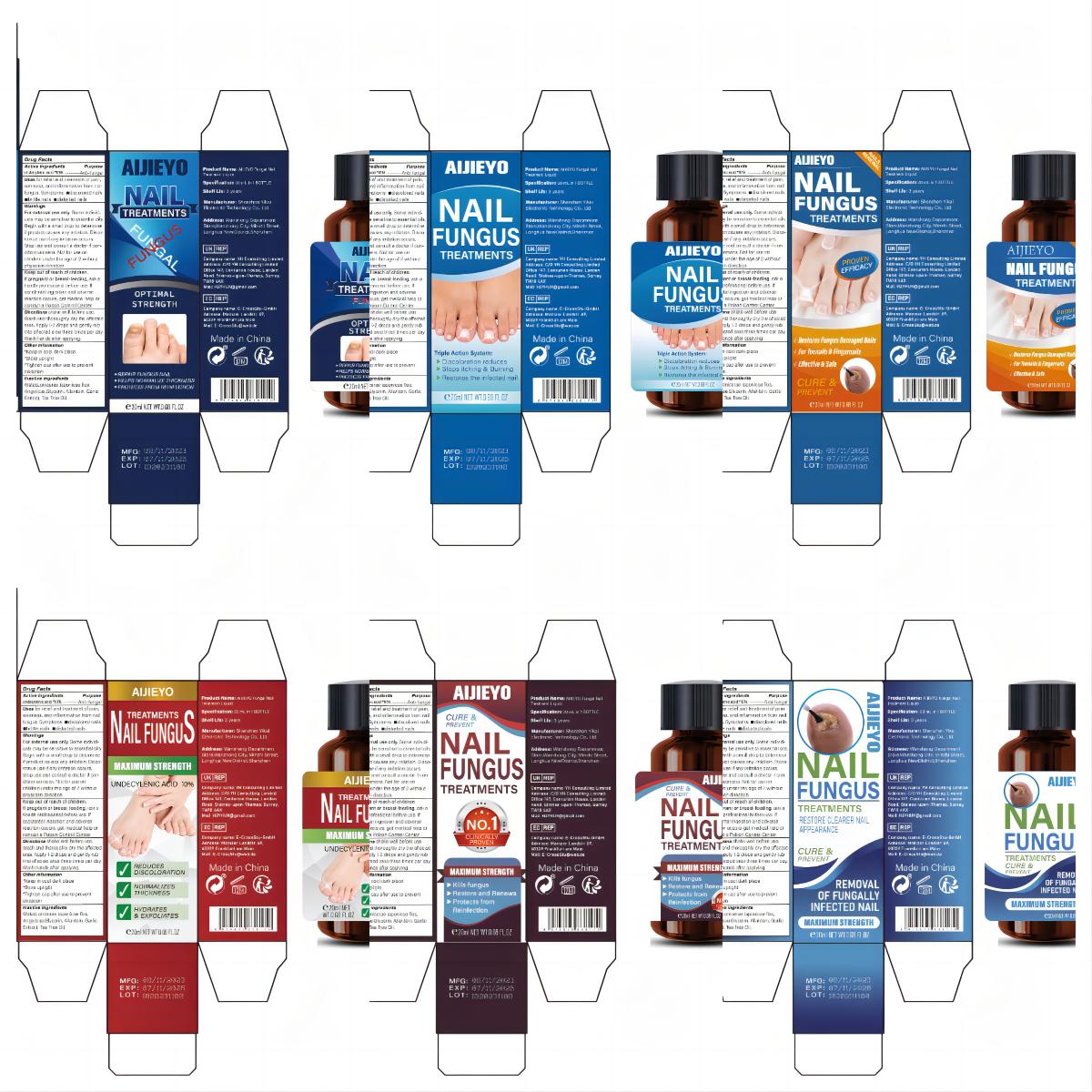 DRUG LABEL: AlJIEYO Fungal Nail Treatment Liquid
NDC: 83809-015 | Form: LIQUID
Manufacturer: Shenzhen Yikai Electronic Technology Co., Ltd.
Category: otc | Type: HUMAN OTC DRUG LABEL
Date: 20231227

ACTIVE INGREDIENTS: UNDECYLENIC ACID 10 g/100 mL
INACTIVE INGREDIENTS: WATER; GLYCERIN; ANGELICA SINENSIS ROOT; GARLIC; LONICERA JAPONICA FLOWER; ALLANTOIN; TEA TREE OIL

83809-015

Active Ingredient

Undecylenic acid 10%

Purpose

Anti-fungal

Use

for relief and treatment of pain,
soreness, and inflammation from nail
fungus. Symptoms:

■discolored nails
■brittle nails

■distorted nails

Warnings

For external use only. Some individuals may be sensitive to essential oils. Begin with a small drop to determine if product causes any irritation. Discontinue use if any irritation occurs. Stop use and consult a doctor if condition worsens. Not for use on children under the age of 2 without physician direction.

Keep Oot Of Reach Of Children

If pregnant or breast-feeding, ask a health professional before use. If accidental ingestion and adverse reaction occurs, get medical help or contact a Poison Control Center.

Directions

shake well before use. Wash and thoroughly dry the affected area. Apply 1-2 drops and gently rub into affected area three times per day. Wash hands after applying.

Other information

*Keep in cool dark place
*Store upright
*Tighten cap after use to prevent
oxidation

Inactive ingredients

Water,Lonicerae Japonicae flos,Angelicae,Glycerin, Allantoin, Garlic Extract, Tea Tree Oil.